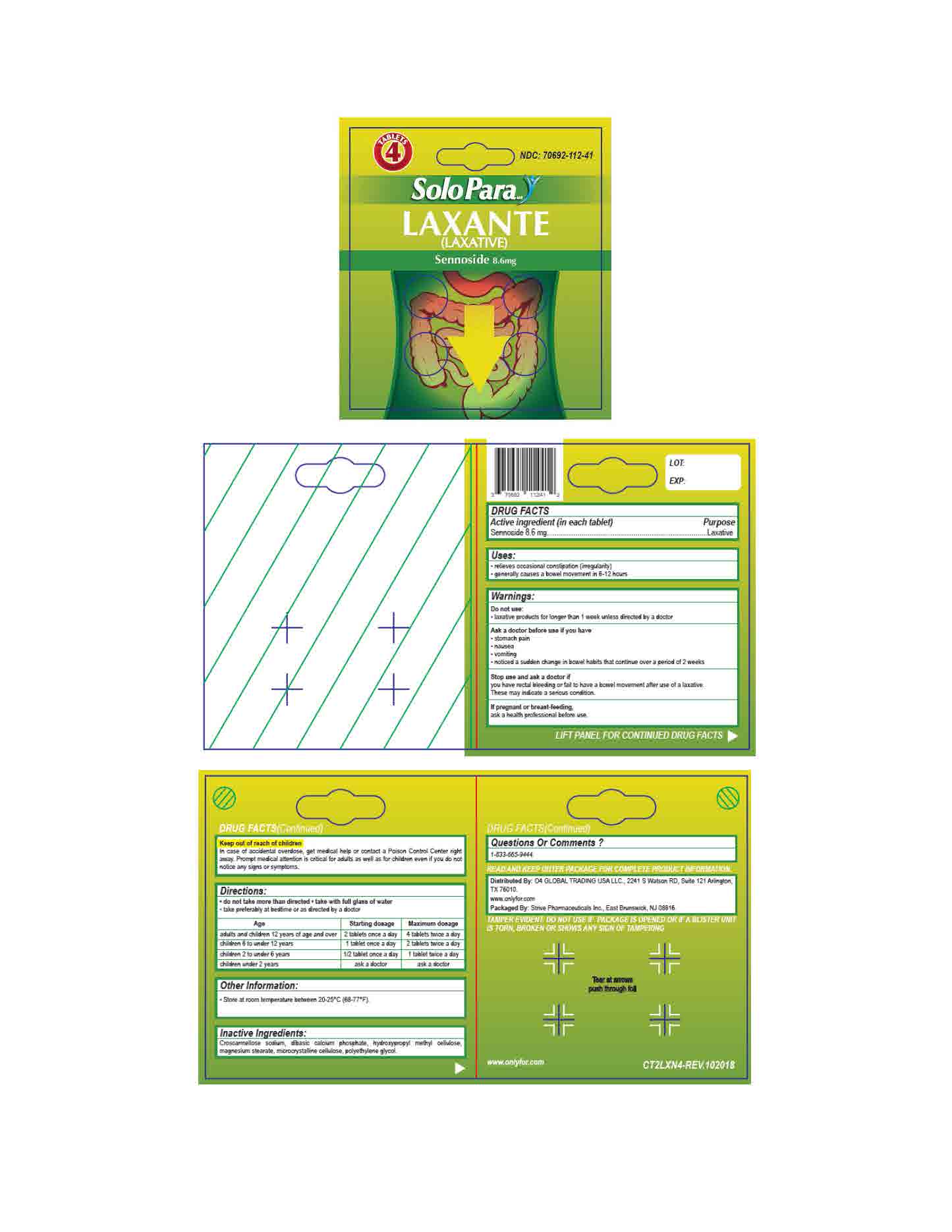 DRUG LABEL: Sennoside 8.6mg
NDC: 70692-112 | Form: TABLET, FILM COATED
Manufacturer: Strive Pharmaceuticals Inc.
Category: otc | Type: HUMAN OTC DRUG LABEL
Date: 20201116

ACTIVE INGREDIENTS: SENNOSIDES A AND B 8.6 mg/1 1
INACTIVE INGREDIENTS: CELLULOSE, MICROCRYSTALLINE; CROSCARMELLOSE SODIUM; DIBASIC CALCIUM PHOSPHATE DIHYDRATE; MAGNESIUM STEARATE; POLYETHYLENE GLYCOL 400; HYPROMELLOSES

Laxative - Laxante (Sennoside 8.6mg)

ACTIVE INGREDIENT

Sennoside 8.6mg

INACTIVE INGREDIENT

croscarmellose sodium, dibasic calcium phosphate, hydroxypropyl methyl cellulose, magnesium stearate, polyethylene glycol

DOSAGE AND ADMINISTRATION

- do not take more than directed
- take with full glass of water
- take preferably at bedtime or as directed by a doctor

Age | Starting dosage | Maximum dosage
adults and children 12 years of age and over | 2 tablets once a day | 4 tablets twice a day
children 6 to under 12 years | 1 tablet once a day | 2 tablets twice a day
children 2 to under 6 years | 1/2 tablet once a day | 1 tablet twice a day
children under 2 years | ask a doctor | ask a doctor

INDICATIONS AND USAGE

- relieves occasional constipation (irregularity)
- generally causes a bowel movement in 6-12 hours

Do not use

laxative products for longer than 1 week unless directed by a doctor

Ask a doctor before use if you have

- stomach pain
- nausea
- vomiting
- notice a sudden change in bowel habits that continue over a period of 2 weeks

Stop use and ask a doctor if

you have rectal bleeding or fail to have a bowel movement after use of a laxative. These may indicate a serious condition.

If pregnant or breast-feeding

ask a health professional before use

Keep out of reach of children

Overdose Warning: In case of accidental overdose, get medical help or contact a Poison Control Center right away. Prompt medical attention is critical for adults as well as for children even if you do not notice any signs or symptoms

Keep out of reach of children

Incase of accidental overdose, get medical help or contact a Poison Contril Center right away. Prompt medical attention is critical for adults as well as for children even if you do not notice any signs or symptoms.

PURPOSE

Laxative

OTHER SAFETY INFORMATION

- Store at room temperature between 20ºC - 25ºC (68ºF - 77ºF).